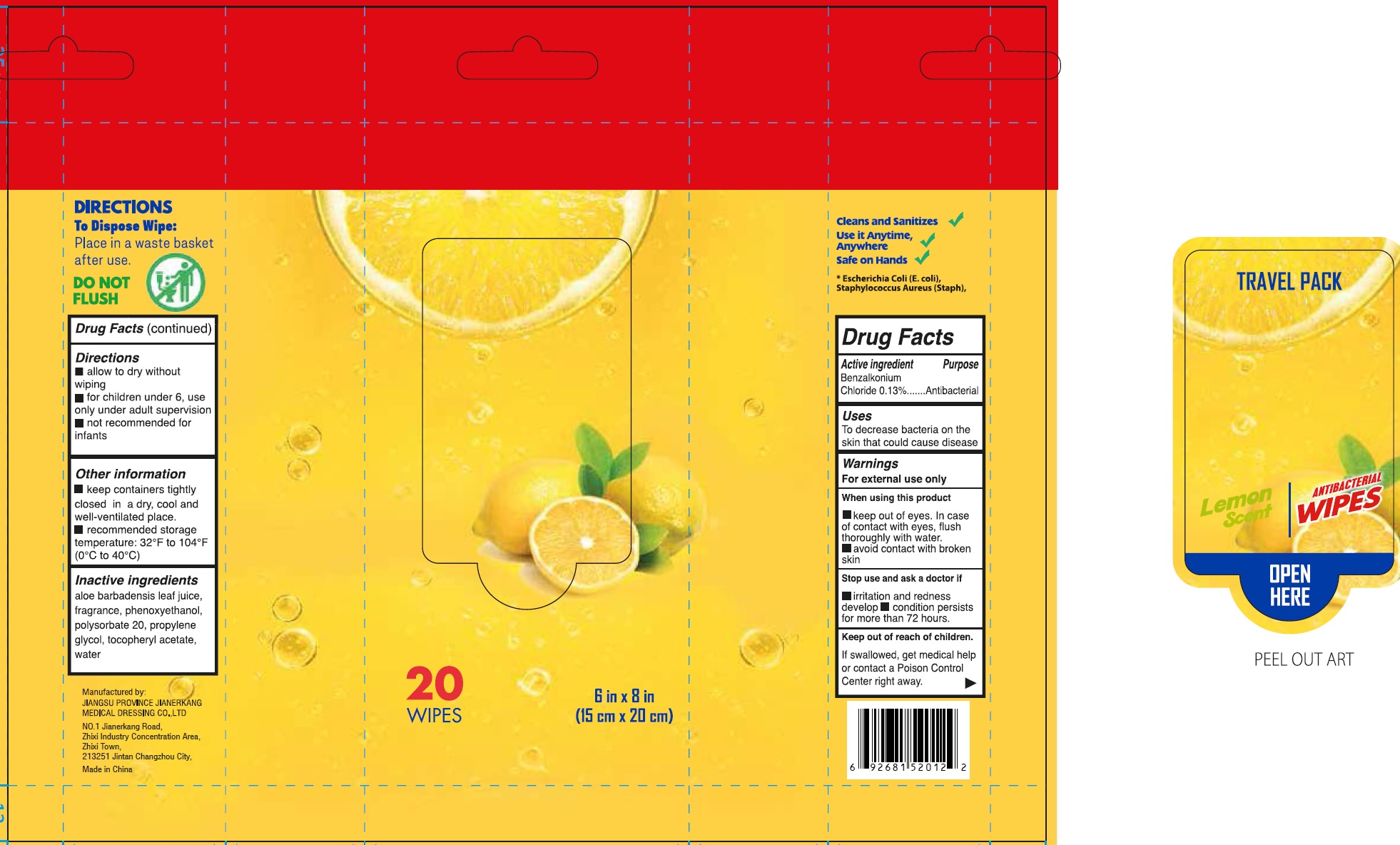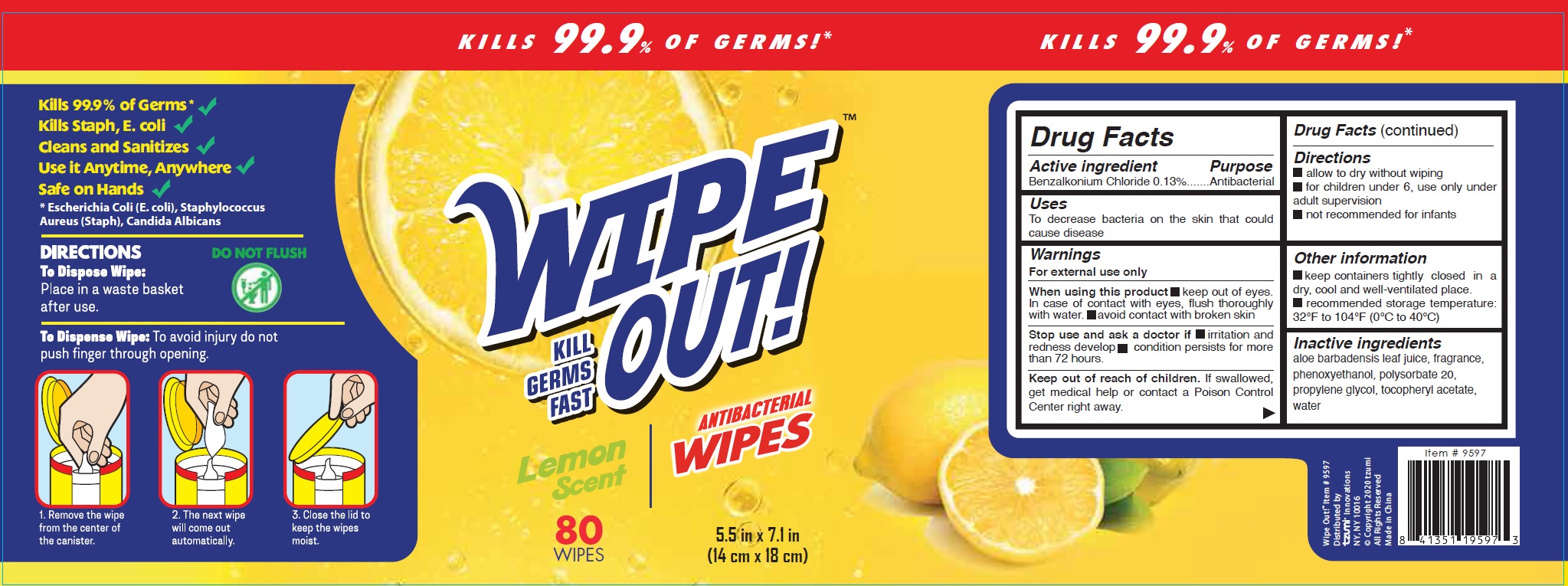 DRUG LABEL: WIPE OUT Antibacterial Wipes, Lemon Scent
NDC: 34645-0009 | Form: CLOTH
Manufacturer: Jianerkang Medical Co., Ltd
Category: otc | Type: HUMAN OTC DRUG LABEL
Date: 20231023

ACTIVE INGREDIENTS: BENZALKONIUM CHLORIDE 1.3 mg/1 mL
INACTIVE INGREDIENTS: ALOE VERA LEAF; PHENOXYETHANOL; POLYSORBATE 20; PROPYLENE GLYCOL; .ALPHA.-TOCOPHEROL ACETATE; WATER

WIPE OUT Antibacterial Wipes, Lemon Scent

Active Ingredient

Benzalkonium Chloride 0.13%

Purpose

Antibacterial

Uses

To decrease bacteria on the skin that could cause disease

Warnings

- For external use only

When using this product

- keep out of eyes. In case of contact with eyes, flush thoroughly with water.
- avoid contact with broken skin

Stop use and ask a doctor if

- irritation and redness develops
- condition persists for more than 72 hours.

Keep out of reach of children.

If swallowed, get medical help or contact a Poison Control Center right away.

Directions

- allow to dry without wiping
- for children under 6, use only under adult supervision
- not recommended for infants

Other Information

- keep containers tightly closed in a dry, cool and well-ventilated place.
- recommended storage temperature: 32°F to 104°F (0°C to 40°C)

Inactive Ingredients

aloe barbadensis leaf juice, fragrance, phenoxyethanol, polysorbate 20, propylene glycol, tocopheryl acetate, water